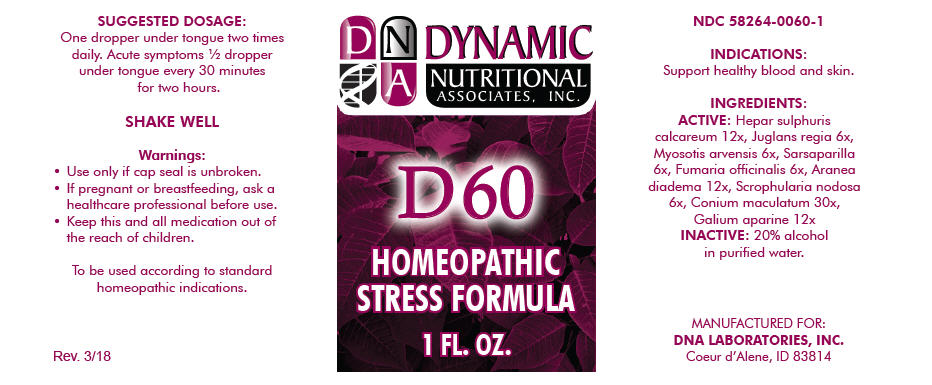 DRUG LABEL: D-60
NDC: 58264-0060 | Form: SOLUTION
Manufacturer: DNA Labs, Inc.
Category: homeopathic | Type: HUMAN OTC DRUG LABEL
Date: 20250113

ACTIVE INGREDIENTS: FUMARIA OFFICINALIS FLOWERING TOP 6 [hp_X]/1 mL; ARANEUS DIADEMATUS 12 [hp_X]/1 mL; SCROPHULARIA NODOSA 6 [hp_X]/1 mL; CONIUM MACULATUM FLOWERING TOP 30 [hp_X]/1 mL; GALIUM APARINE 12 [hp_X]/1 mL; CALCIUM SULFIDE 12 [hp_X]/1 mL; JUGLANS REGIA FRUIT RIND, IMMATURE 6 [hp_X]/1 mL; JUGLANS REGIA LEAF 6 [hp_X]/1 mL; MYOSOTIS ARVENSIS 6 [hp_X]/1 mL; SMILAX ORNATA ROOT 6 [hp_X]/1 mL
INACTIVE INGREDIENTS: ALCOHOL; WATER

D-60

NDC 58264-0060-1

INDICATIONS

PURPOSE

Support healthy blood and skin.

INGREDIENTS

ACTIVE

Hepar sulphuris calcareum 12x, Juglans regia 6x, Myosotis arvensis 6x, Sarsaparilla 6x, Fumaria officinalis 6x, Aranea diadema 12x, Scrophularia nodosa 6x, Conium maculatum 30x, Galium aparine 12x

INACTIVE

20% alcohol in purified water.

SUGGESTED DOSAGE

One dropper under tongue two times daily. Acute symptoms ½ dropper under tongue every 30 minutes for two hours.

STORAGE AND HANDLING

SHAKE WELL

Warnings

- Use only if cap seal is unbroken.

PREGNANCY OR BREAST FEEDING

- If pregnant or breastfeeding, ask a healthcare professional before use.

KEEP OUT OF REACH OF CHILDREN

- Keep this and all medication out of the reach of children.

To be used according to standard homeopathic indications.

PRINCIPAL DISPLAY PANEL - 1 FL. OZ. Bottle Label

DYNAMIC
NUTRITIONAL
ASSOCIATES, INC.

D 60

HOMEOPATHIC
STRESS FORMULA

1 FL. OZ.